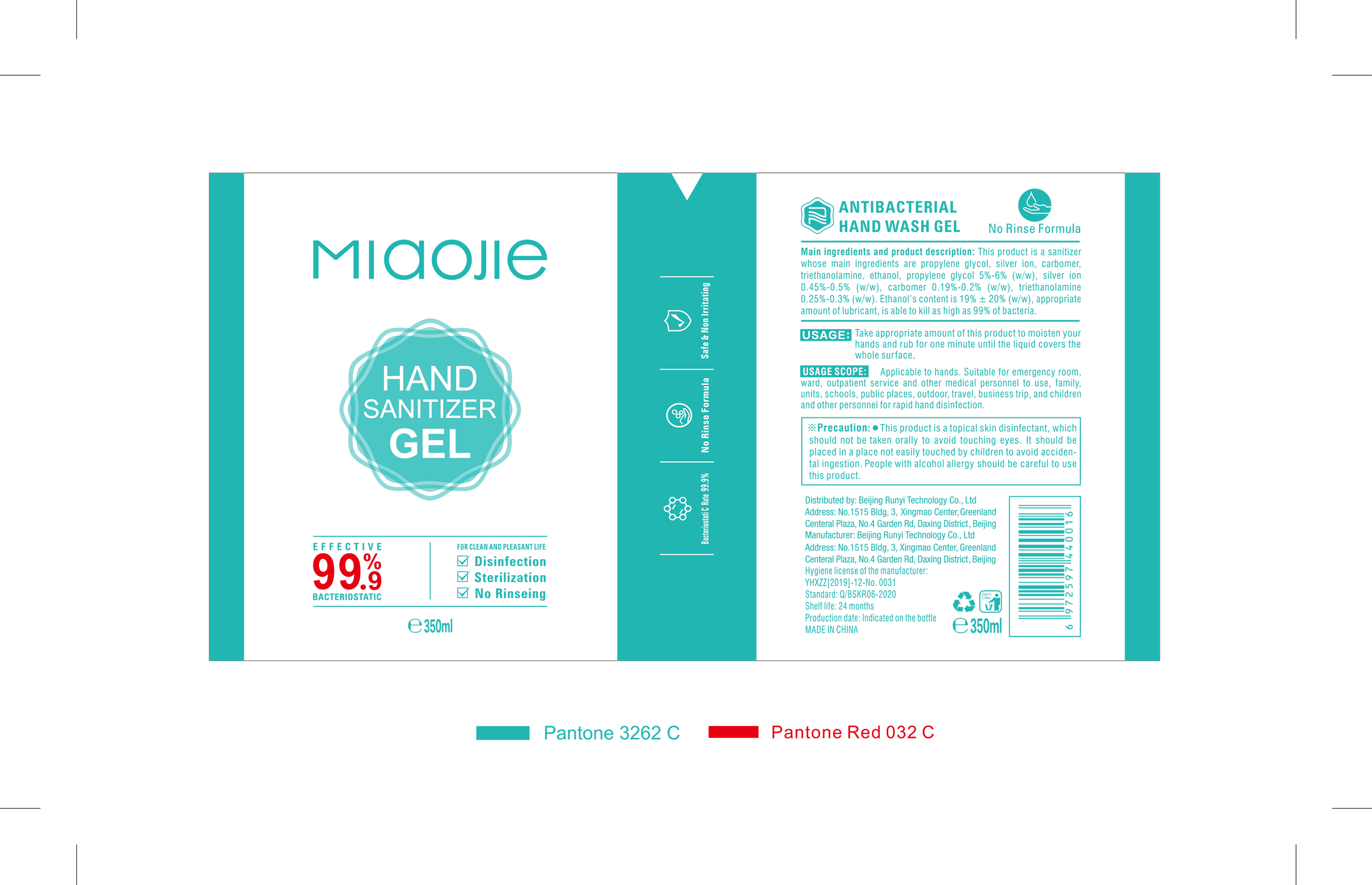 DRUG LABEL: RUNYI MIAOJIE Hand sanitizer
NDC: 41500-002 | Form: LIQUID
Manufacturer: Beijing Runyi Technology Co., Ltd
Category: otc | Type: HUMAN OTC DRUG LABEL
Date: 20200512

ACTIVE INGREDIENTS: ALCOHOL 66.5 mL/350 mL; CARBOMER HOMOPOLYMER, UNSPECIFIED TYPE 0.665 mg/350 mL; SILVER CATION 1.75 mg/350 mL; TROLAMINE 1.05 mg/350 mL; PROPYLENE GLYCOL 17.5 mg/350 mL
INACTIVE INGREDIENTS: WATER

DOSAGE AND ADMINISTRATION

Colorless transparent gel.

WARNINGS

This product is a topical skin disinfectant, which should not be taken orally to avoid touching eyes. It should be placed in a place not easily touched by children to avoid acciden-tal ingestion. People with alcohol alrgy should be careful to use this product.

INACTIVE INGREDIENT

Water

INDICATIONS AND USAGE

Take appropriate amount of this product to moisten your hands and rub for one minute until the liquid covers the whole surface.

KEEP OUT OF REACH OF CHILDREN

It should be placed in a place not easily touched by children to avoid acciden-tal ingestion.

PURPOSE

Disinfection
Sterilization
No Rinseing

ACTIVE INGREDIENT

propylene glycol, silver ion, carbomer, triethanolamine, ethanol